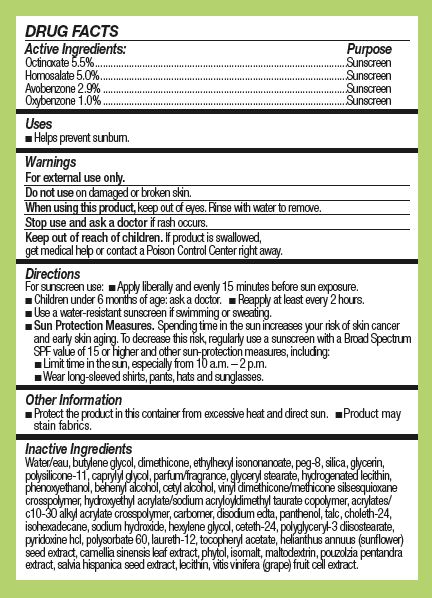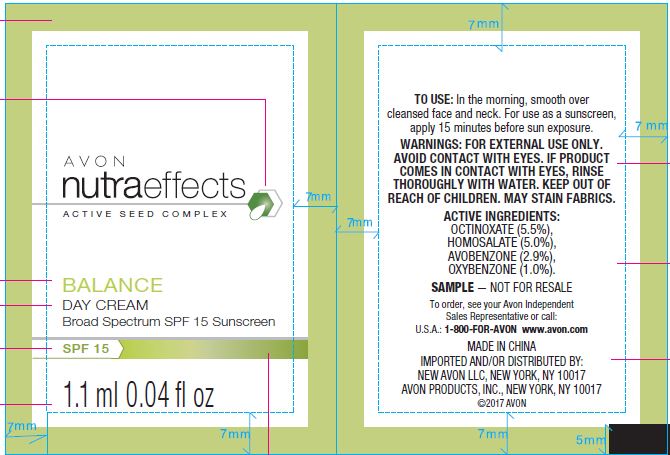 DRUG LABEL: Avon Nutra Effects
NDC: 71110-0015 | Form: CREAM
Manufacturer: Avon Products, Inc.
Category: otc | Type: HUMAN OTC DRUG LABEL
Date: 20180601

ACTIVE INGREDIENTS: OCTINOXATE 55 mg/1 g; HOMOSALATE 50 mg/1 g; AVOBENZONE 29 mg/1 g; OXYBENZONE 10 mg/1 g
INACTIVE INGREDIENTS: ETHYLHEXYL ISONONANOATE; CETYL ALCOHOL; VINYL DIMETHICONE/METHICONE SILSESQUIOXANE CROSSPOLYMER; TALC; CHOLETH-24; HEXYLENE GLYCOL; CETETH-24; POLYSORBATE 60; WATER; GLYCERIN; ISOHEXADECANE; PANTHENOL; MALTODEXTRIN; PHYTOL; SODIUM HYDROXIDE; DIMETHICONE; PHENOXYETHANOL; CAPRYLYL GLYCOL; BUTYLENE GLYCOL; POLYGLYCERYL-3 DIISOSTEARATE; ISOMALT; LAURETH-12

Active Ingredients:

Octinoxate 5.5%......

Homosalate 5.0%....

Avonbenzone 2.9%.....

Oxybenzone 1.0%......

Purpose

............Sunscreen

............Sunscreen

............Sunscreen

............Sunscreen

Uses

Helps prevent sunburn.

Warnings

For external use only.

Do not use on damaged or broken skin.

When using this product, keep out of eyes. Rinse with water to remove.

Stop use and ask a doctor if rash occurs.

KEEP OUT OF REACH OF CHILDREN

Keep our of reach of children. If product is swallowed, get medical help or contact a Poison Control Center right away.

Directions

For suncreen use:

Apply liberally and evenly 15 minutes before sun exposure.
Children under 6 months of age: ask a doctor.
Reapply at least every 2 hours.
Use a water-resistant sunscreen if swimming or sweating.
Sun Protection Measures. Spending time in the sun increases your risk of skin cancer and early skin aging. To decrease this risk, regularly use a sunscreen with a Broad Spectrum SPF value of 15 or higher and other sun-procteion measures, including:
Limite time in the sun, expecially from 10 a.m.-2 p.m.
Wear long-sleeved shirts, pants, hats and sunglasses.

Other Information

- Protect the product in this container from excessive heat and direct sun,
- Product may stain fabrics.

Inactive ingredients

WATER/EAU, BUTYLENE GLYCOL, DIMETHICONE, ETHYLHEXYL ISONONANOATE, PEG-8, SILICA, GLYCERIN, POLYSILICONE-11, CAPRYLYL GLYCOL, PARFUM/FRAGRANCE, GLYCERYL STEARATE, HYDROGENATED LECITHIN, PHENOXYETHANOL, BEHENYL ALCOHOL, CETYL ALCOHOL, VINYL DIMETHICONE/METHICONE SILSESQUIOXANE CROSSPOLYMER, HYDROXYETHYL ACRYLATE/SODIUM ACRYLOYLDIMETHYL TAURATE COPOLYMER, ACRYLATES/C10-30 ALKYL ACRYLATE CROSSPOLYMER, CARBOMER, DISODIUM EDTA, PANTHENOL, TALC, CHOLETH-24, ISOHEXADECANE, SODIUM HYDROXIDE, HEXYLENE GLYCOL, CETETH-24, POLYGLYCERYL-3 DIISOSTEARATE, PYRIDOXINE HCL, POLYSORBATE 60, LAURETH-12, TOCOPHERYL ACETATE, HELIANTHUS ANNUUS (SUNFLOWER) SEED EXTRACT, CAMELLIA SINENSIS LEAF EXTRACT, PHYTOL, ISOMALT, MALTODEXTRIN, POUZOLZIA PENTANDRA EXTRACT, SALVIA HISPANICA SEED EXTRACT, LECITHIN, VITIS VINIFERA (GRAPE) FRUIT CELL EXTRACT.